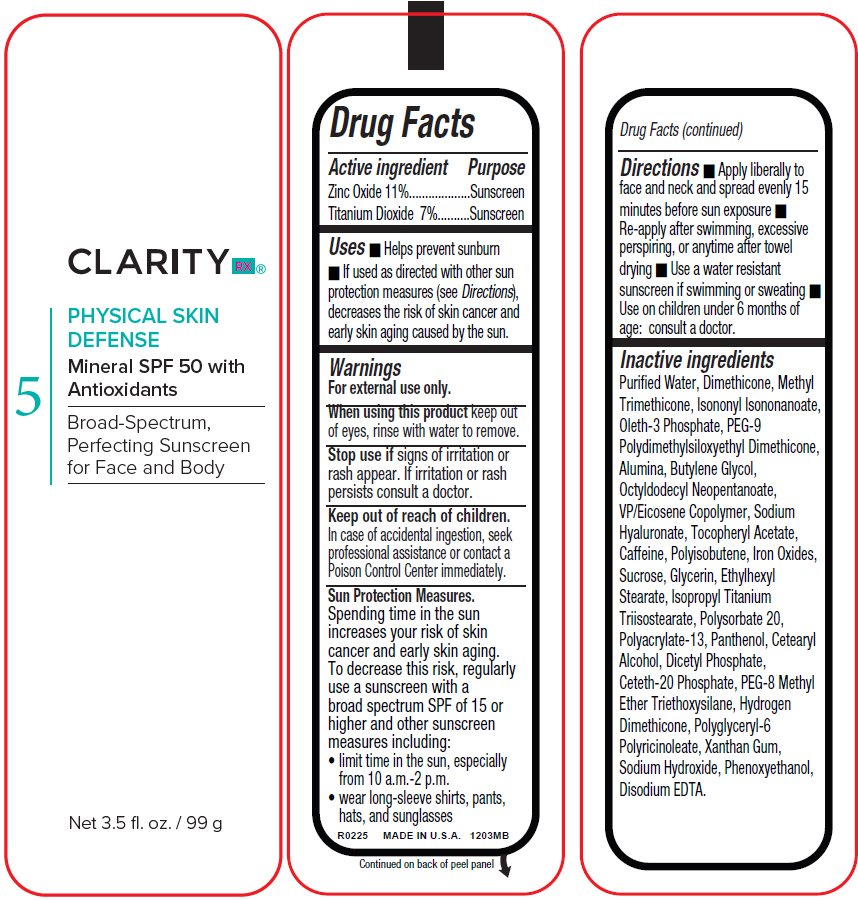 DRUG LABEL: Clarity Rx Physical Skin Defense
NDC: 51326-035 | Form: LOTION
Manufacturer: Topiderm, Inc.
Category: otc | Type: HUMAN OTC DRUG LABEL
Date: 20250410

ACTIVE INGREDIENTS: ZINC OXIDE 110 mg/1 g; TITANIUM DIOXIDE 75 mg/1 g
INACTIVE INGREDIENTS: WATER; DIMETHICONE; METHYL TRIMETHICONE; ISONONYL ISONONANOATE; OLETH-3 PHOSPHATE; PEG-9 POLYDIMETHYLSILOXYETHYL DIMETHICONE; ALUMINUM OXIDE; BUTYLENE GLYCOL; OCTYLDODECYL NEOPENTANOATE; VINYLPYRROLIDONE/EICOSENE COPOLYMER; HYALURONATE SODIUM; .ALPHA.-TOCOPHEROL ACETATE; CAFFEINE; POLYSORBATE 20; SODIUM ACRYLATE/SODIUM ACRYLOYLDIMETHYLTAURATE COPOLYMER (4000000 MW); DEXPANTHENOL; CETOSTEARYL ALCOHOL; DIHEXADECYL PHOSPHATE; CETETH-20 PHOSPHATE; TRIETHOXYSILANE; XANTHAN GUM; SODIUM HYDROXIDE; PHENOXYETHANOL; EDETATE DISODIUM

Clarity Rx® Physical Skin Defense
SPF 50

Drug Facts

ACTIVE INGREDIENT

Active ingredient | Purpose
Zinc Oxide 11% | Sunscreen
Titanium Dioxide 7% | Sunscreen

Uses

- Helps prevent sunburn
- If used as directed with other sun protection measures (see Directions), decreases the risk of skin cancer and early skin aging caused by the sun.

Warnings

For external use only.

When using this product keep out of eyes, rinse with water to remove.

Stop use if signs of irritation or rash appear. If irritation or rash persists consult a doctor.

Keep out of reach of children.

In case of accidental ingestion, seek professional assistance or contact a Poison Control Center immediately.

Sun Protection Measures.

Spending time in the sun increases your risk of skin cancer and early skin aging.

To decrease this risk, regularly use a sunscreen with a broad spectrum SPF of 15 or higher and other sunscreen measures including:

- limit time in the sun, especially from 10 a.m.-2 p.m.
- wear long-sleeve shirts, pants, hats, and sunglasses

Directions

- Apply liberally to face and neck and spread evenly 15 minutes before sun exposure
- Re-apply after swimming, excessive perspiring, or anytime after towel drying
- Use a water resistant sunscreen if swimming or sweating
- Use on children under 6 months of age: consult a doctor.

Inactive ingredients

Puriﬁed Water, Dimethicone, Methyl Trimethicone, Isononyl Isononanoate, Oleth-3 Phosphate, PEG-9 Polydimethylsiloxyethyl Dimethicone, Alumina, Butylene Glycol, Octyldodecyl Neopentanoate, VP/Eicosene Copolymer, Sodium Hyaluronate, Tocopheryl Acetate, Caffeine, Polyisobutene, Iron Oxides, Sucrose, Glycerin, Ethylhexyl Stearate, Isopropyl Titanium Triisostearate, Polysorbate 20, Polyacrylate-13, Panthenol, Cetearyl Alcohol, Dicetyl Phosphate, Ceteth-20 Phosphate, PEG-8 Methyl Ether Triethoxysilane, Hydrogen Dimethicone, Polyglyceryl-6 Polyricinoleate, Xanthan Gum, Sodium Hydroxide, Phenoxyethanol, Disodium EDTA.

PRINCIPAL DISPLAY PANEL - 99 g Bottle Label

CLARITY RX®

5
PHYSICAL SKIN
DEFENSE

Mineral SPF 50 with
Antioxidants

Broad-Spectrum,
Perfecting Sunscreen
for Face and Body

Net 3.5 fl. oz. / 99 g